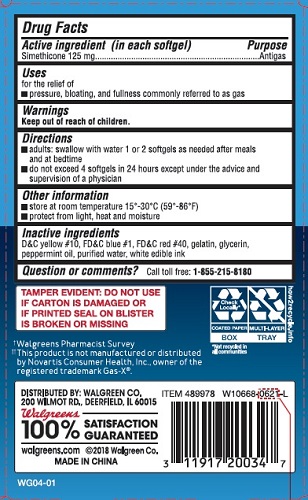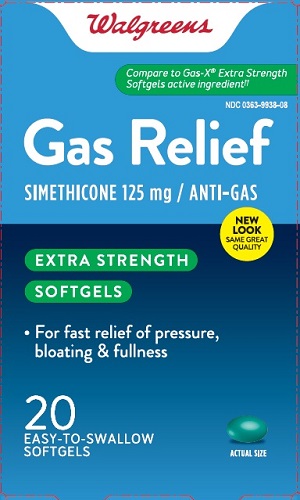 DRUG LABEL: Gas Relief
NDC: 0363-9938 | Form: CAPSULE, LIQUID FILLED
Manufacturer: Walgreen Co.
Category: otc | Type: HUMAN OTC DRUG LABEL
Date: 20241121

ACTIVE INGREDIENTS: DIMETHICONE 125 mg/1 1
INACTIVE INGREDIENTS: D&C YELLOW NO. 10; FD&C BLUE NO. 1; FD&C RED NO. 40; GELATIN; GLYCERIN; PEPPERMINT OIL; WATER

Extra Strength Gas Relief

Drug Facts

Active ingredient (in each softgel)

Simethicone 125 mg

Purpose

Antigas

Uses

for the relief of

- pressure, bloating, and fullness commonly referred to as gas

Warnings

Keep out of reach of children.

Directions

- adults: swallow with water 1 or 2 softgels as needed after meals and at bedtime
- do not exceed 4 softgels in 24 hours except under the advice and supervision of a physician

Other information

- store at room temperature 15°-30°C (59°-86°F)
- protect from light, heat and moisture

Inactive ingredients

D&C yellow #10, FD&C blue #1, FD&C red #40, gelatin, glycerin, peppermint oil, purified water, white edible ink

Questions or comments?

Call toll free: 1-855-215-8180

PRINCIPAL DISPLAY PANEL

EXTRA STRENGTH GAS RELIEF

SIMETHICONE 125 mg ANTI-GAS 20 Softgels

NDC 0363-9938-08

*Compare to the active ingredient in Gas-X®Extra Strength Softgels